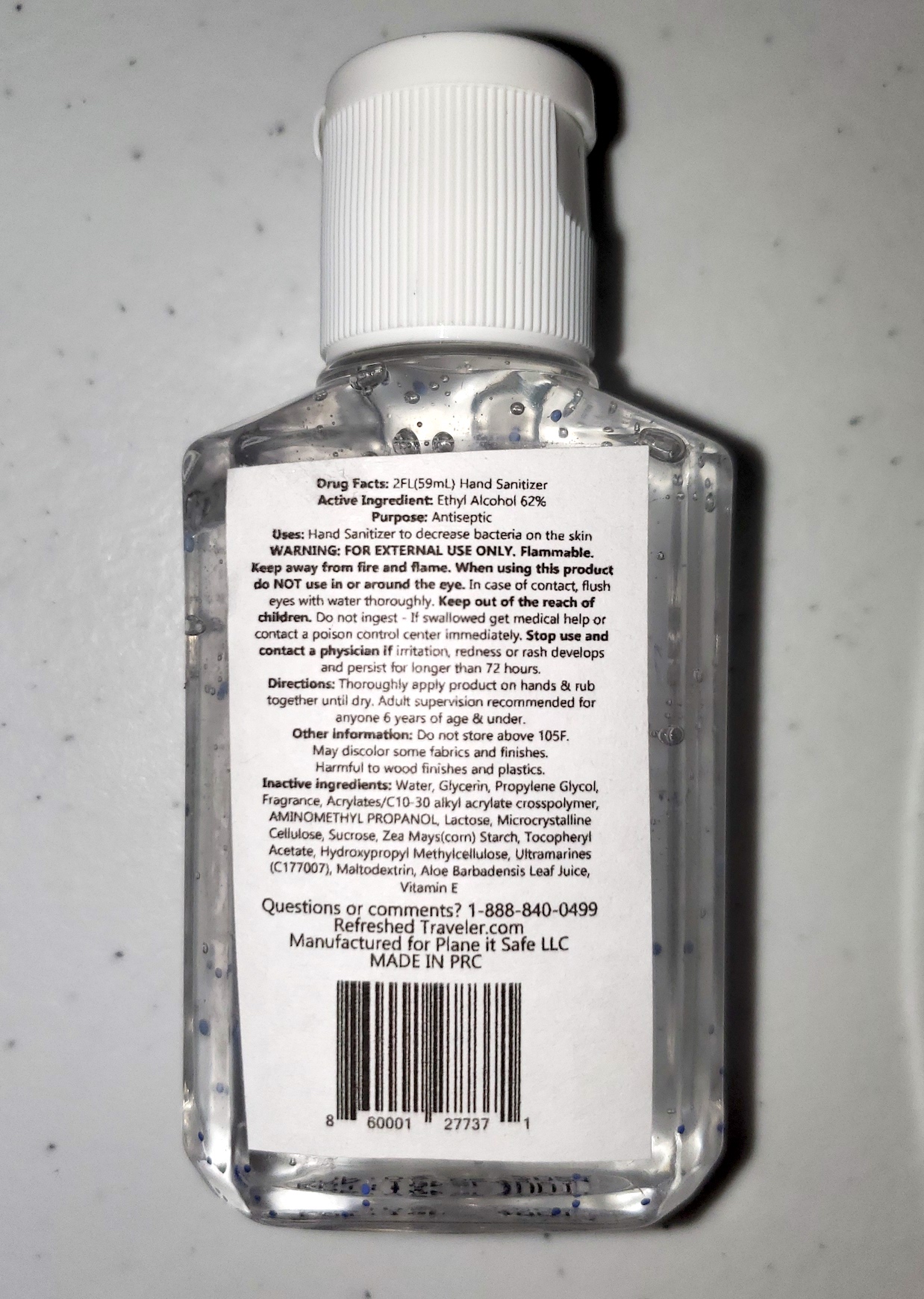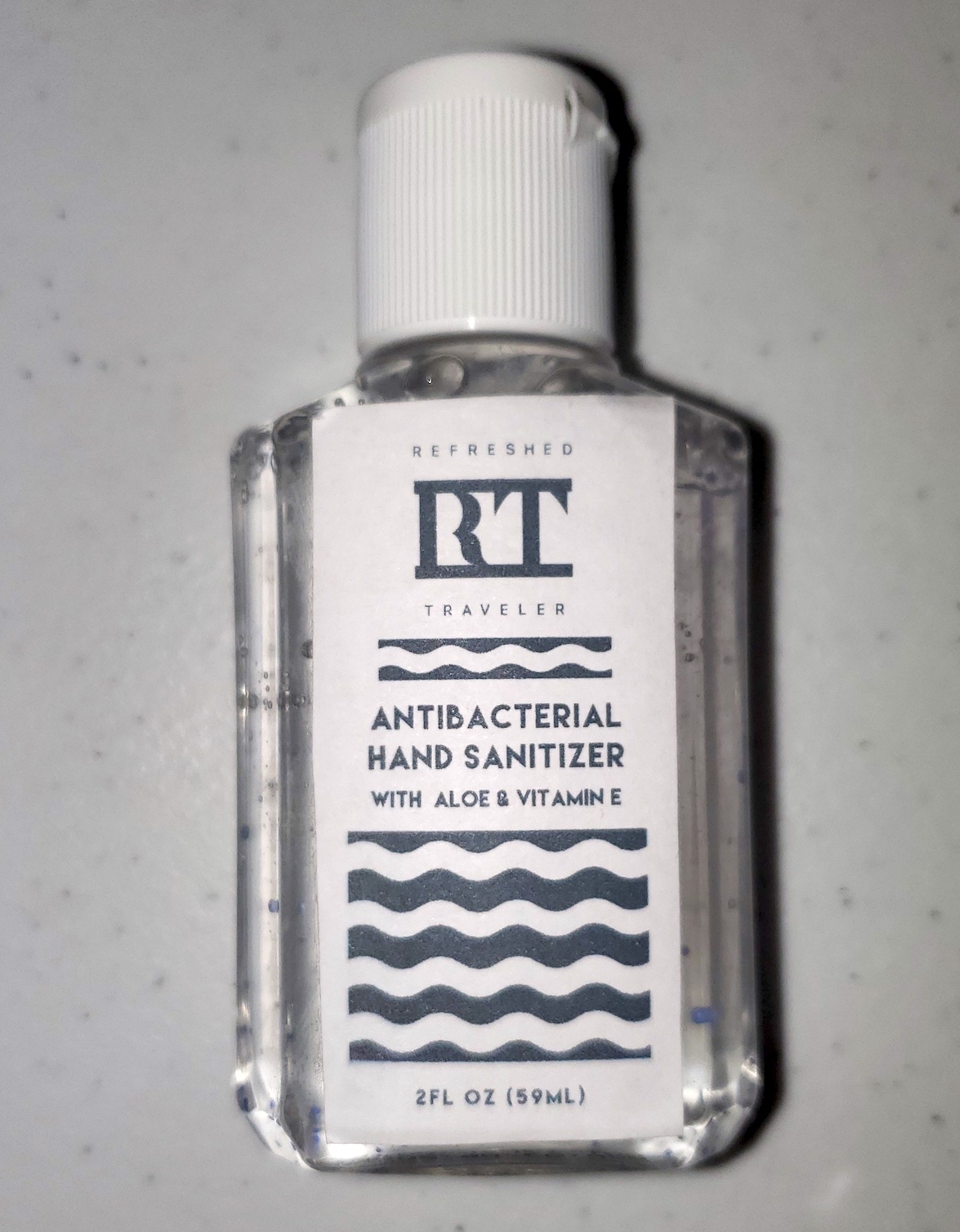 DRUG LABEL: Refreshed Traveler Hand Sanitizer
NDC: 72920-2011 | Form: GEL
Manufacturer: Hand Sanitizer
Category: otc | Type: HUMAN OTC DRUG LABEL
Date: 20211224

ACTIVE INGREDIENTS: ALCOHOL 62 mL/100 mL
INACTIVE INGREDIENTS: WATER

Refreshed Traveler Hand Sanitizer

Warning

FOR EXTERNAL USE ONLY

Active Ingredients

Ethyl Alcohol

KEEP OUT OF REACH OF CHILDREN

Do not ingest - If swallowed get medical help or contact a poison control center immediately

STOP USE

Stop and contact a physician if irritation, redness, or rash develops and persist for longer than 72 hours

PURPOSE

Antiseptic to decrease bacteria on the skin

Directions

Throughly apply product on hands and rub together until dry. Adult supervision recommended for anyone under 6 years of age.

INACTIVE INGREDIENT

Water, Glycerin, Proptlene Glycol, Fragrance, Acrylates/C10-30 alkyl acrylate crosspolymer, Aminomethyl Propanol, Lactose, Microcrystalline Cellulose, Sucrose, Zea Mays (corn) Starch, Tocopheryl Acetate, Hydroxypropyl, Methylcellulose, Ultramarines (C177007), Maltodextrin, Aloe Barbadensis Leaf Juice, Vitamin E

WHEN USING

Hand sanitizer to decrease bacteria on the skin

INDICATIONS AND USAGE

Hand sanitizer to decrease bacteria on the hands